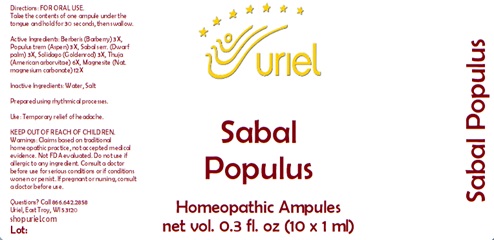 DRUG LABEL: Sabal Populus
NDC: 48951-8161 | Form: LIQUID
Manufacturer: Uriel Pharmacy Inc.
Category: homeopathic | Type: HUMAN OTC DRUG LABEL
Date: 20241205

ACTIVE INGREDIENTS: BERBERIS VULGARIS ROOT BARK 3 [hp_X]/1 mL; POPULUS TREMULA WHOLE 3 [hp_X]/1 mL; SAW PALMETTO 3 [hp_X]/1 mL; SOLIDAGO VIRGAUREA FLOWERING TOP 3 [hp_X]/1 mL; THUJA OCCIDENTALIS WHOLE 6 [hp_X]/1 mL; MAGNESITE 12 [hp_X]/1 mL
INACTIVE INGREDIENTS: SODIUM CHLORIDE; WATER

Sabal Populus

INDICATIONS AND USAGE

Directions: FOR ORAL USE.

DOSAGE AND ADMINISTRATION

Take the contents of one ampule under the tongue and hold for 30 seconds, then swallow.

ACTIVE INGREDIENT

Active Ingredients: Berberis (Barberry) 3X, Populus trem (Aspen) 3X, Sabal serr. (Dwarf palm) 3X, Solidago (Goldenrod) 3X, Thuja (American arborvitae) 6X, Magnesite (Nat. magnesium carbonate) 12X

Inactive Ingredients: Water, Salt

Prepared using rhythmical processes.

PURPOSE

Use: Temporary relief of headache.

KEEP OUT OF REACH OF CHILDREN.

WARNINGS

Warnings: Claims based on traditional homeopathic practice, not accepted medical evidence. Not FDA evaluated. Do not use if allergic to any ingredient. Consult a doctor before use for serious conditions or if conditions worsen or persist. If pregnant or nursing, consult a doctor before use.

QUESTIONS

Questions? Call 866.642.2858 Uriel, East Troy, WI 53120 shopuriel.com Lot: